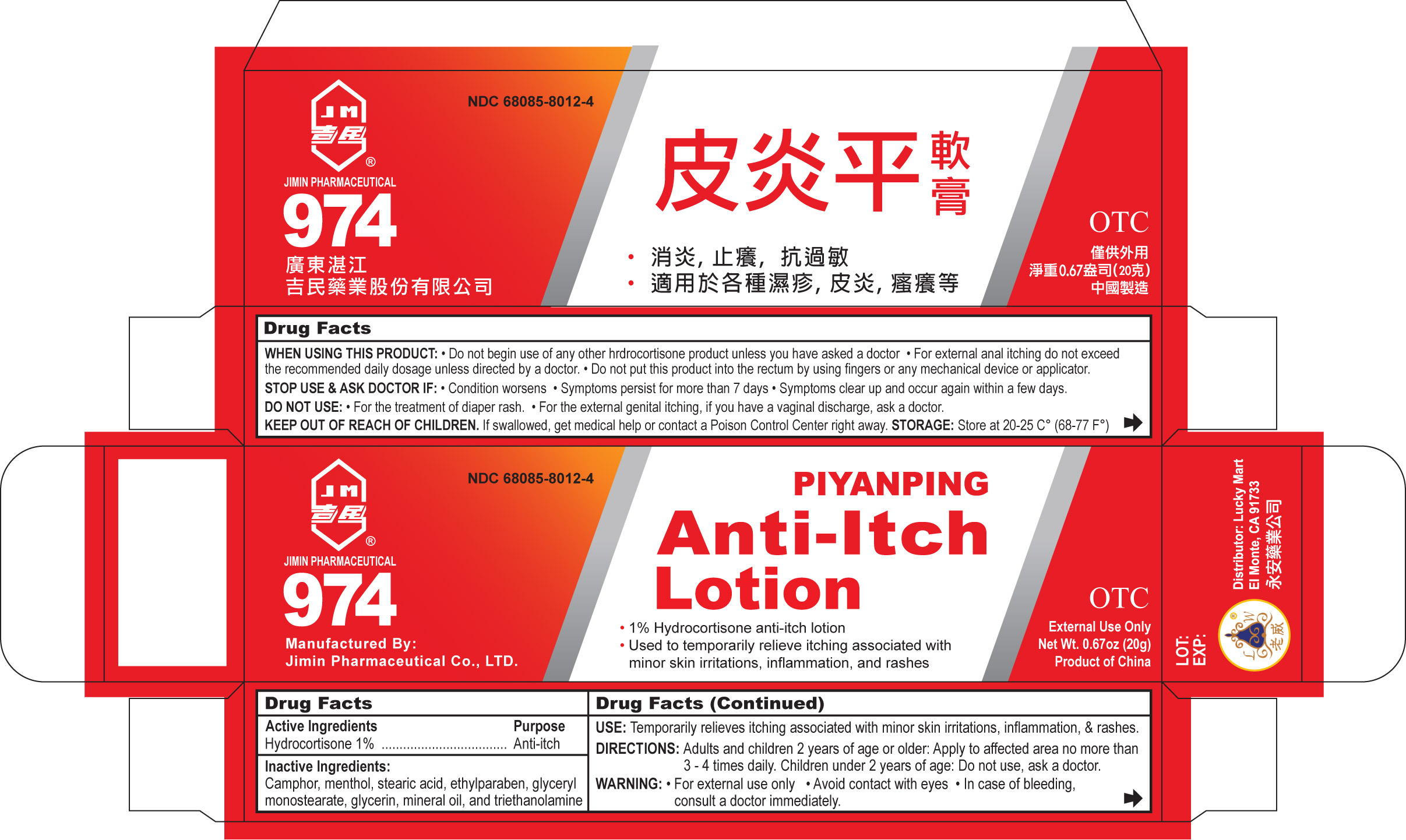 DRUG LABEL: Piyanping antiitch
NDC: 68085-8012 | Form: CREAM
Manufacturer: Guangdong Zhanjiang Jimin Pharmaceutical Company, Ltd.
Category: otc | Type: HUMAN OTC DRUG LABEL
Date: 20120130

ACTIVE INGREDIENTS: Hydrocortisone 1 g/100 g
INACTIVE INGREDIENTS: camphor (synthetic); menthol; stearic acid; ethylparaben; glyceryl monostearate; glycerin; mineral oil; trolamine

Piyanpingantiitch

STORAGE AND HANDLING

Storage: Store at 20-25 C (68-77 F)

INACTIVE INGREDIENT

Inactive ingredients: camphor, menthol, stearic acid, ethylparaben, glyceryl monostearate, glycerin, mineral oil, and triethanolamine

Stop use and ask a doctor if
• Condition worsens
• Symptoms persist for more than 7 days or clear up and occur again within a few days

Keep out the reach of children
If swallowed, get medical help or contact a Poison Control Center right away.

Do not use
• For the treatment of diaper rash. Ask a doctor.
• For the external genital itching, if you have a vaginal discharge, ask a doctor.

PURPOSE

ANTI-ITCH

When using this product
• Avoid contact with eyes
• Do not begin use of any other hrdrocortisone product unless you have asked a doctor
• For external anal itching do not exceed the recommended daily dosage unless directed by a doctor. In case of bleeding, consult a doctor promptly.
• Do not put this product into the rectum by using fingers or any mechanical device or applicator

Active ingredient Purpose
Hydrocortisone 1%........................... Anti-itch

Uses
temporarily relieve itching associated with minor skin irritations, inflammation, and rashes

Warnings - For external use only

Directions
adults and children 2 years of age and older:
• Apply to affected area no more than 3-4 times daily
Children under 2 years of age:
• Do not use, ask a doctor

PACKAGE LABEL

PIYANGING ANTI-ITCH LOTION
1% HYDROCORTISONE ANTI-ITCH LOTION
Uses to temporarily relieve itching associated with minor skin irritations, inflammation, and rashes
For external use only
Product of China
Net wt. 0.67 oz. (20g)